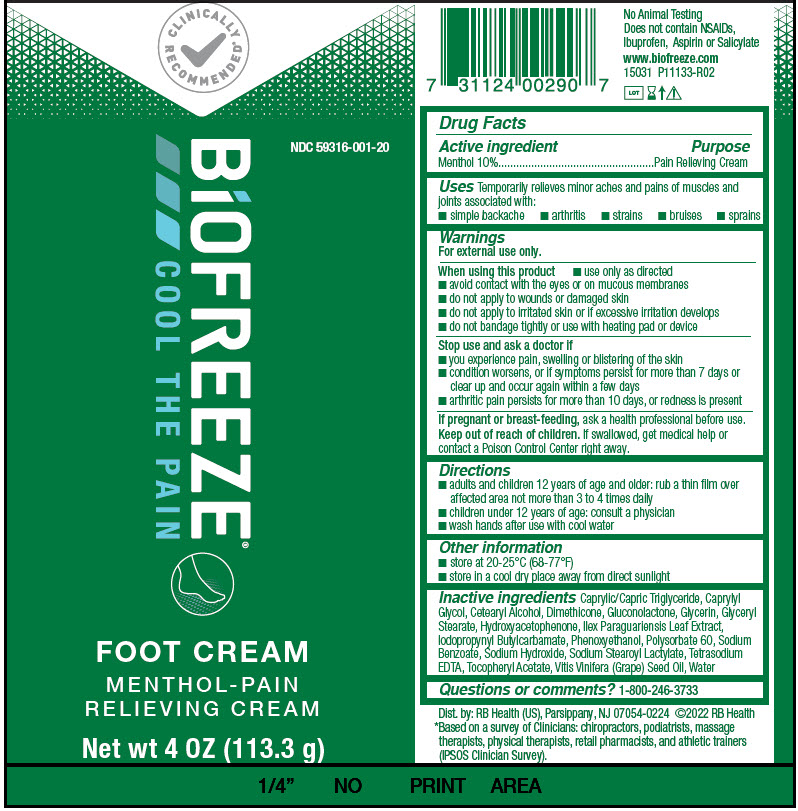 DRUG LABEL: Biofreeze Foot Cream
NDC: 59316-001 | Form: CREAM
Manufacturer: RB Health (US) LLC
Category: otc | Type: HUMAN OTC DRUG LABEL
Date: 20241227

ACTIVE INGREDIENTS: MENTHOL, UNSPECIFIED FORM 100 mg/1 g
INACTIVE INGREDIENTS: MEDIUM-CHAIN TRIGLYCERIDES; CAPRYLYL GLYCOL; CETOSTEARYL ALCOHOL; DIMETHICONE; GLUCONOLACTONE; GLYCERIN; GLYCERYL MONOSTEARATE; HYDROXYACETOPHENONE; ILEX PARAGUARIENSIS LEAF; IODOPROPYNYL BUTYLCARBAMATE; PHENOXYETHANOL; POLYSORBATE 60; SODIUM BENZOATE; SODIUM HYDROXIDE; SODIUM STEAROYL LACTYLATE; EDETATE SODIUM; .ALPHA.-TOCOPHEROL ACETATE; GRAPE SEED OIL; WATER

Biofreeze®Foot Cream

Drug Facts

Active ingredient

Menthol 10%

Purpose

Pain Relieving Cream

Uses

Temporarily relieves minor aches and pains of muscles and joints associated with:

- simple backache
- arthritis
- strains
- bruises
- sprains

Warnings

For external use only.

When using this product

- use only as directed
- avoid contact with the eyes or on mucous membranes
- do not apply to wounds or damaged skin
- do not apply to irritated skin or if excessive irritation develops
- do not bandage tightly or use with heating pad or device

Stop use and ask a doctor if

- you experience pain, swelling or blistering of the skin
- condition worsens, or if symptoms persist for more than 7 days or clear up and occur again within a few days
- arthritic pain persists for more than 10 days, or redness is present

PREGNANCY OR BREAST FEEDING

If pregnant or breast-feeding,ask a health professional before use.

Keep out of reach of children.If swallowed, get medical help or contact a Poison Control Center right away.

Directions

- adults and children 12 years of age and older: rub a thin film over affected area not more than 3 to 4 times daily
- children under 12 years of age: consult a physician
- wash hands after use with cool water

Other information

- store at 20-25°C (68-77°F)
- store in a cool dry place away from direct sunlight

Inactive ingredients

Caprylic/Capric Triglyceride, Caprylyl Glycol, Cetearyl Alcohol, Dimethicone, Gluconolactone, Glycerin, Glyceryl Stearate, Hydroxyacetophenone, Ilex Paraguariensis Leaf Extract, Iodopropynyl Butylcarbamate, Phenoxyethanol, Polysorbate 60, Sodium Benzoate, Sodium Hydroxide, Sodium Stearoyl Lactylate, Tetrasodium EDTA, Tocopheryl Acetate, Vitis Vinifera (Grape) Seed Oil, Water

Questions or comments?

1-800-246-3733

Dist. by: RB Health (US), Parsippany, NJ 07054-0224

PRINCIPAL DISPLAY PANEL - 113.3 g Tube Label

CLINICALLY
RECOMMENDED*

NDC 59316-001-20

BiOFREEZE®
COOL THE PAIN

FOOT CREAM

MENTHOL-PAIN
RELIEVING CREAM

Net wt 4 OZ (113.3 g)